DRUG LABEL: Unknown
Manufacturer: Food and Drug Administration
Category: other | Type: Indexing - Pharmacologic Class
Date: 20130321

TAFLUPROST Pharmacologic Class Indexing